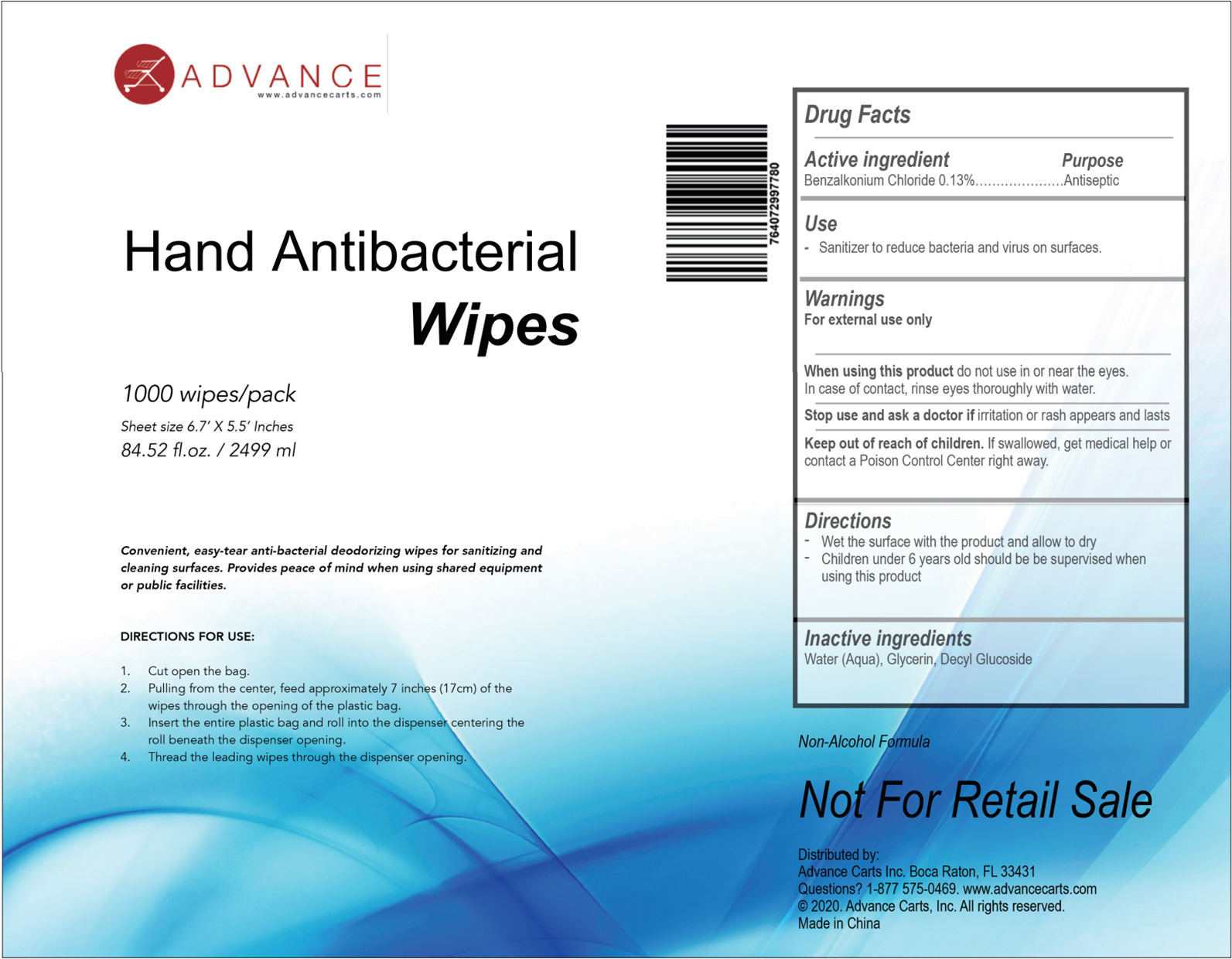 DRUG LABEL: Hand Antibacterial Wipes
NDC: 76991-009 | Form: CLOTH
Manufacturer: Hefei Wenqi Industrial & Trade Co., Ltd
Category: otc | Type: HUMAN OTC DRUG LABEL
Date: 20200624

ACTIVE INGREDIENTS: BENZALKONIUM CHLORIDE 0.13 g/100 mL
INACTIVE INGREDIENTS: DIDECYLDIMONIUM CHLORIDE; GLYCERIN; WATER

Hand Antibacterial Wipes

Active Ingredient(s)

Benzalkonium chloride 0.13%

Purpose

Antiseptic

Use

Sanitizer to reduce bacteria and virus on surfaces

Do not use in or contact the eyes
Discontinue useif irritation and redness develop. if condition persists for more than 72 hours consult a physician.

WHEN USING

Pull through about one inch. Replace cover Pull out wipes as needed and snap off at a 90° angle. Keep cap closed to prevent evaporation
Wipe hands, fingers, interdigital areas and wrists thoroughly with towelette. Be sure to utilize the entire wipe surface, Allow to dry
lf hands are visibly soiled or contaminated use first wipe to clean hands then discard wipe Sanitize with a second wipe discard after single use.

STOP USE

/

keep out of reach of children.
lf swallowed. get medical help or contact a Poison Control Center right away

Directions

Wet the surface with the product and allow to dry
Children under 6 years old should bebe supervised when using this product

Inactive ingredients

decyl glucoside
Glycerin
water